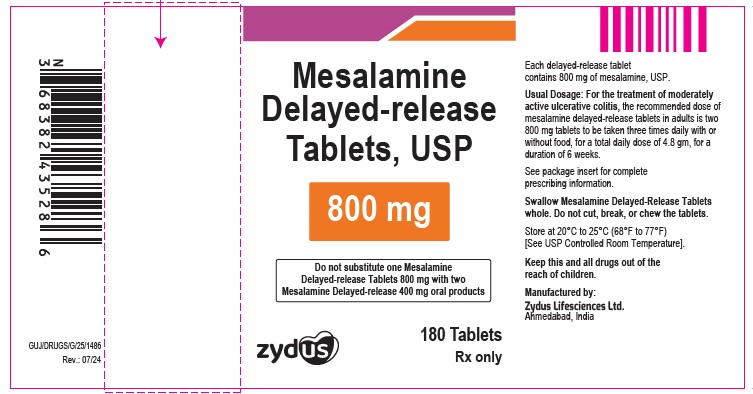 DRUG LABEL: mesalamine
NDC: 70771-1110 | Form: TABLET, DELAYED RELEASE
Manufacturer: Zydus Lifesciences Limited
Category: prescription | Type: HUMAN PRESCRIPTION DRUG LABEL
Date: 20241130

ACTIVE INGREDIENTS: MESALAMINE 800 mg/1 1
INACTIVE INGREDIENTS: ACETYLTRIBUTYL CITRATE; SILICON DIOXIDE; FERRIC OXIDE RED; MAGNESIUM STEARATE; METHACRYLIC ACID; CELLULOSE, MICROCRYSTALLINE; POVIDONE; SODIUM STARCH GLYCOLATE TYPE A POTATO; TALC; TITANIUM DIOXIDE; FERROSOFERRIC OXIDE; ISOPROPYL ALCOHOL; BUTYL ALCOHOL; PROPYLENE GLYCOL; AMMONIA; SHELLAC

MESALAMINE DELAYED-RELEASE TABLETS

PACKAGE LABEL.PRINCIPAL DISPLAY PANEL

NDC 70771-1110-8 in bottle of 180 tablets

Mesalamine Delayed-release Tablets USP, 800 mg

Rx only

180 tablets